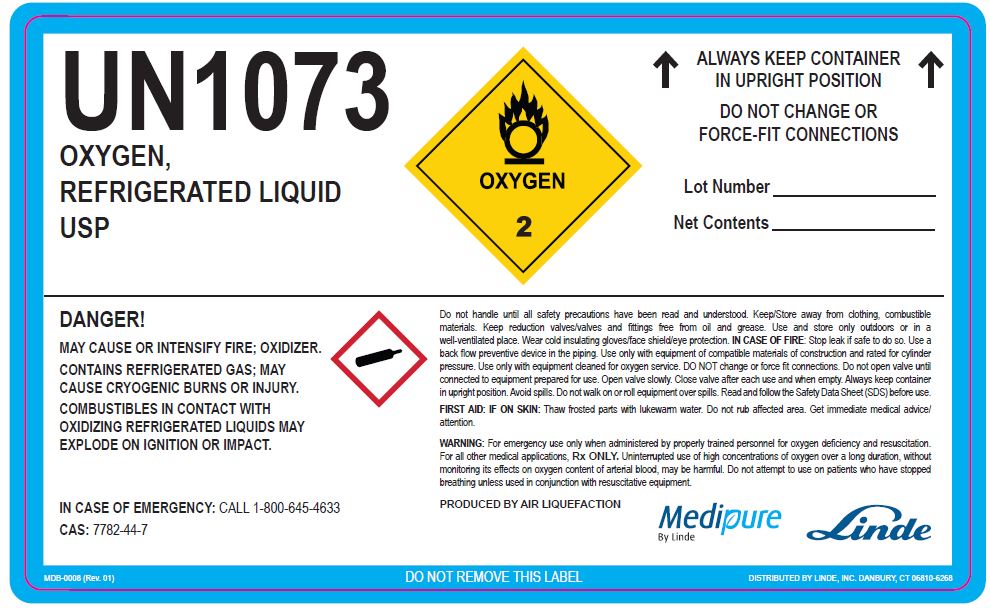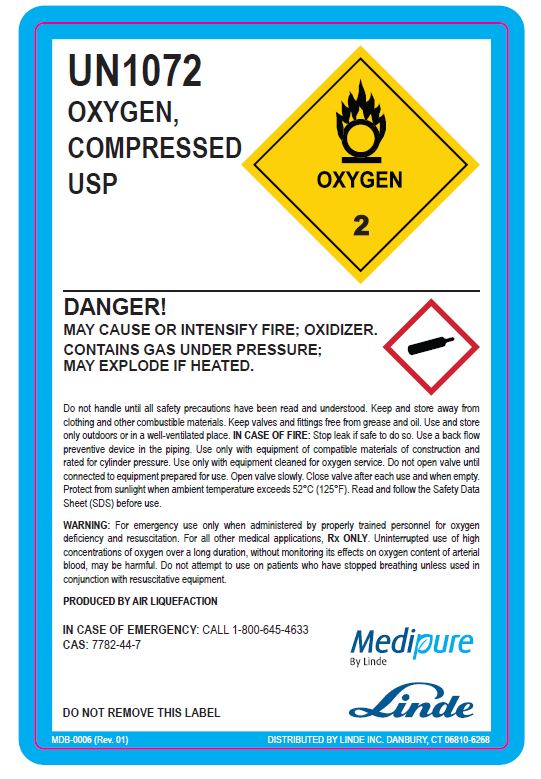 DRUG LABEL: Oxygen
NDC: 11324-001 | Form: GAS
Manufacturer: Linde Puerto Rico B.V.
Category: prescription | Type: HUMAN PRESCRIPTION DRUG LABEL
Date: 20251231

ACTIVE INGREDIENTS: OXYGEN 990 mL/1 L

Oxygen USP Gurabo